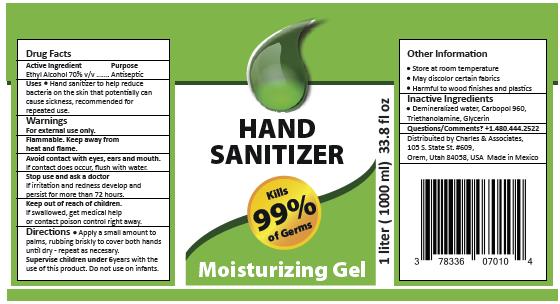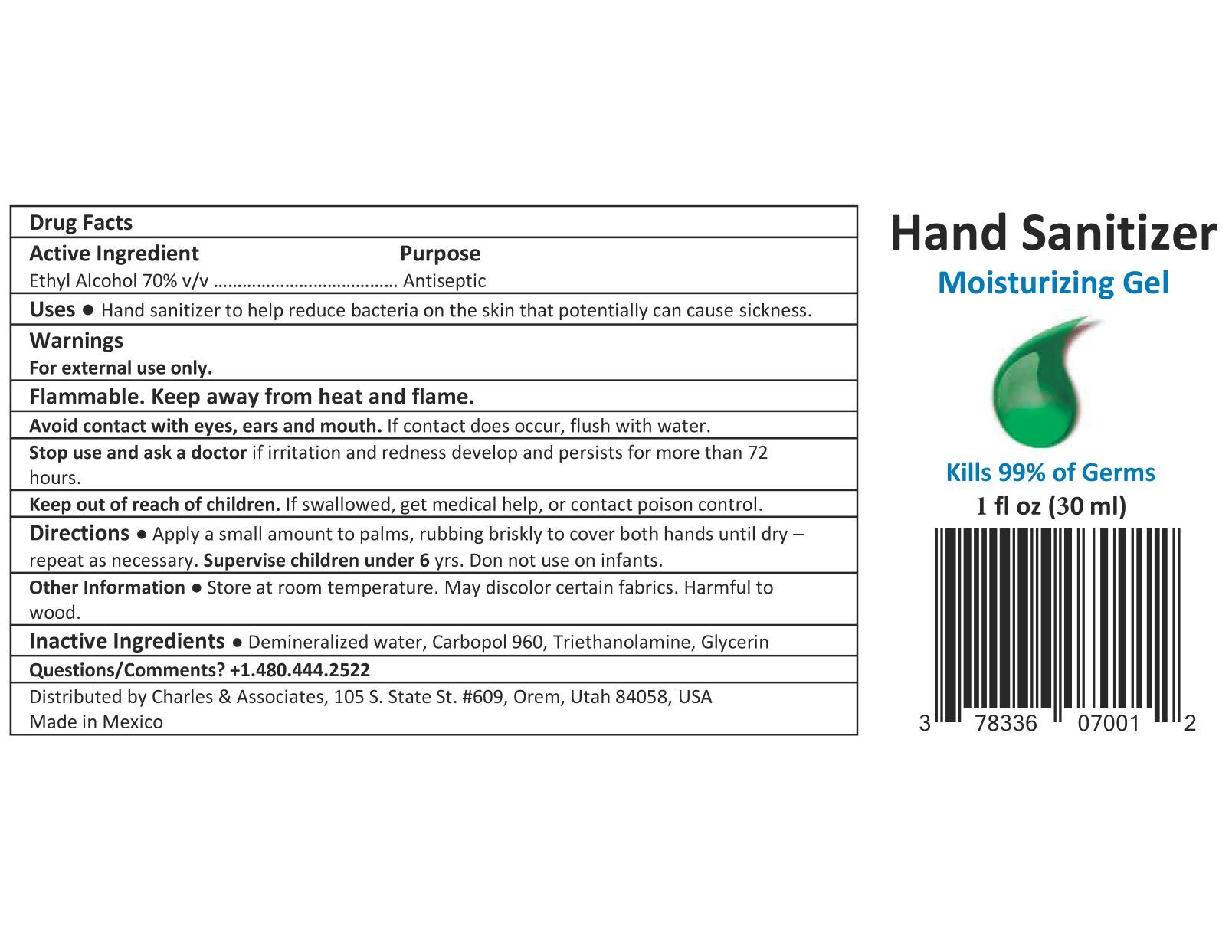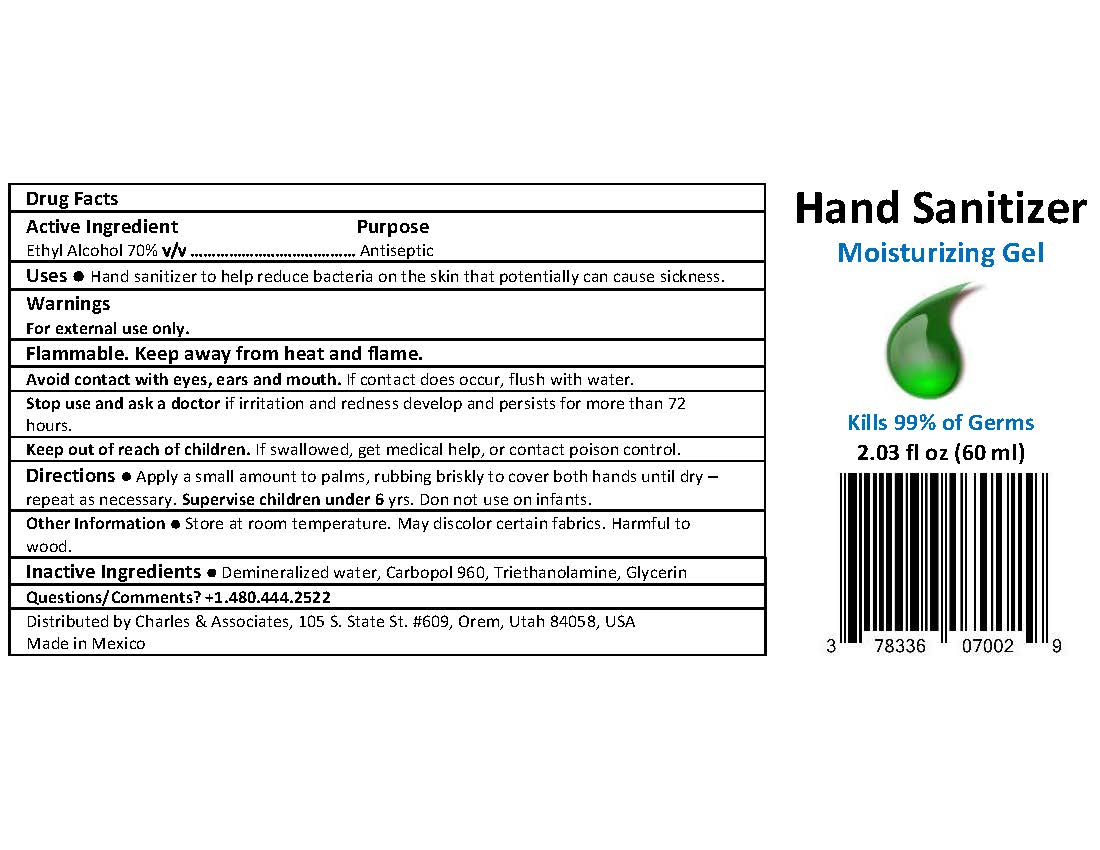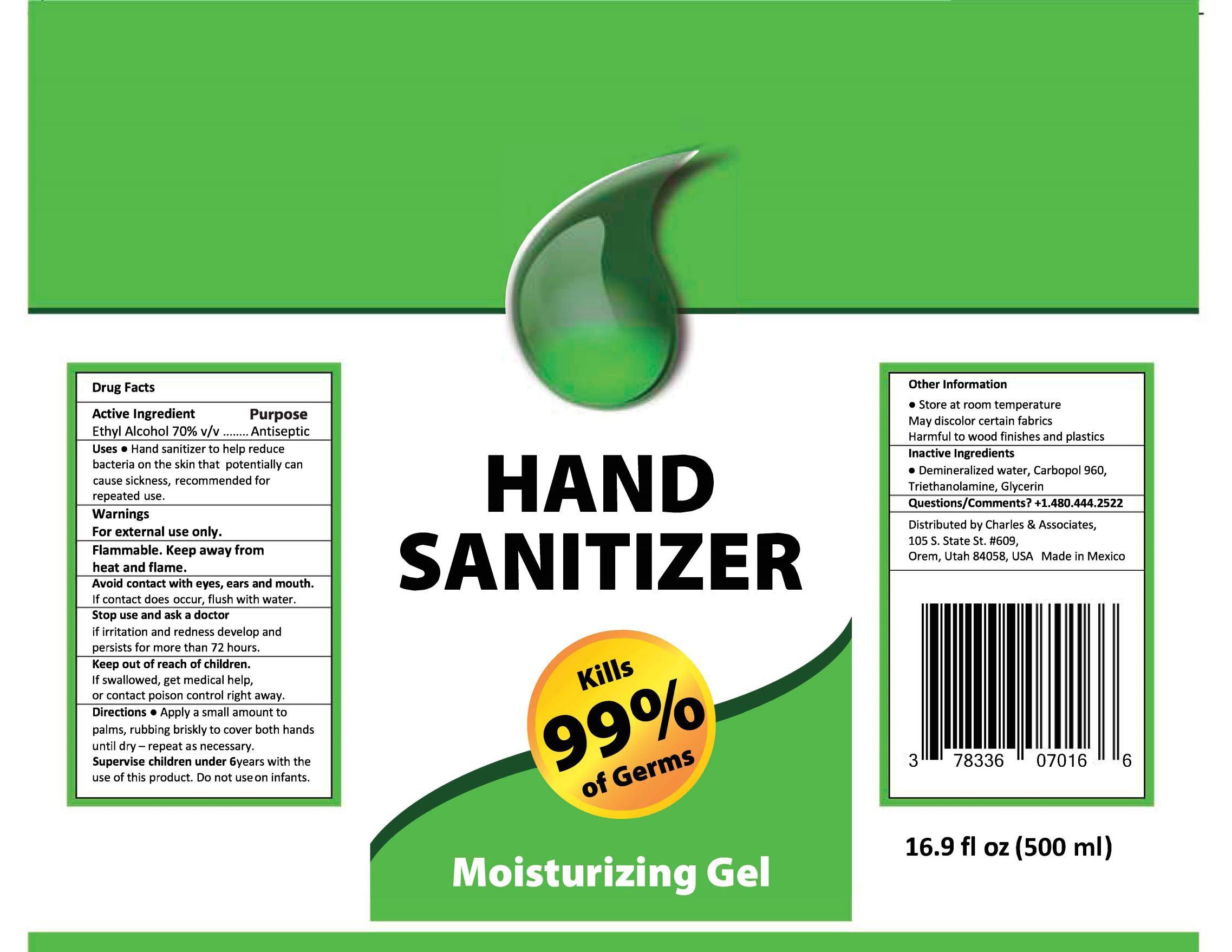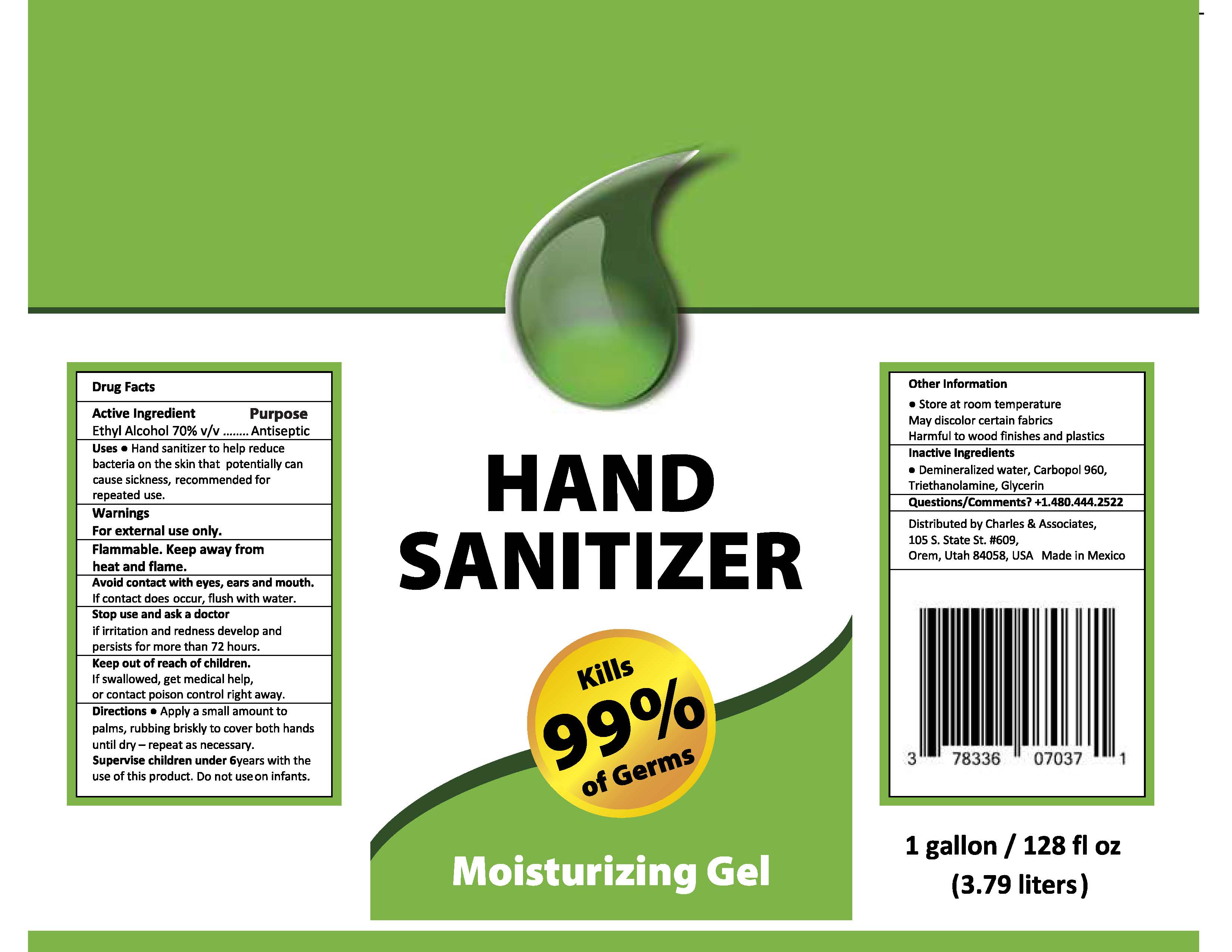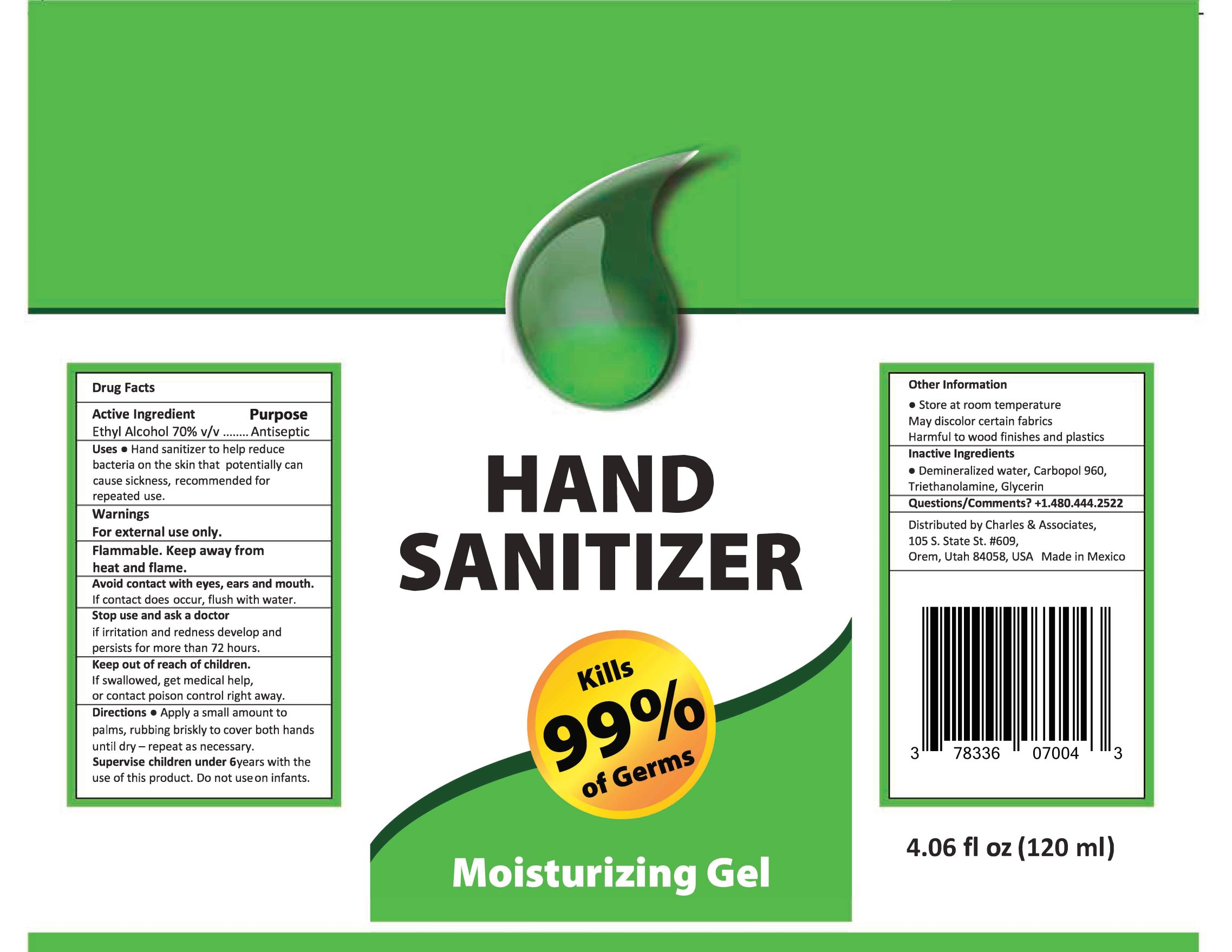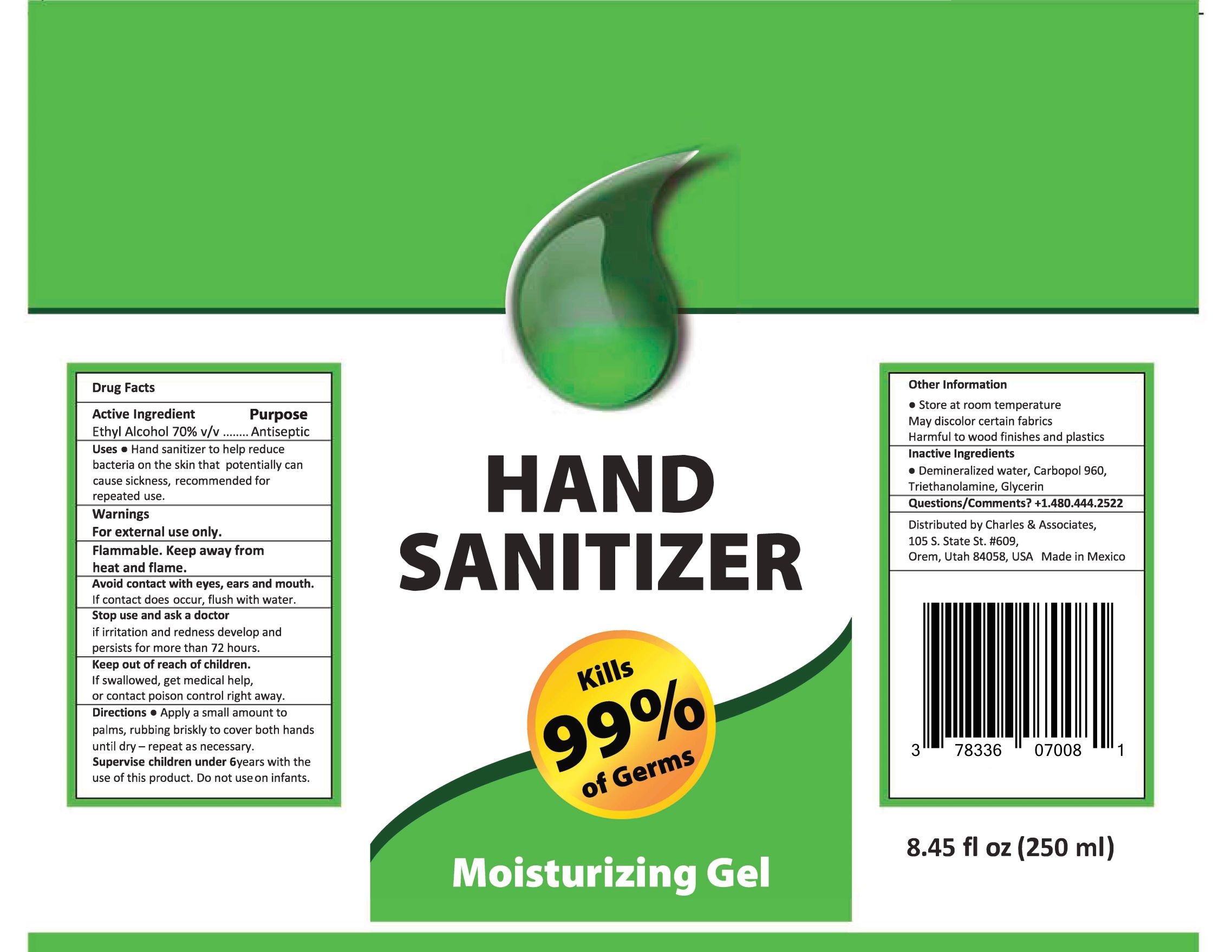 DRUG LABEL: Hand Sanitizer
NDC: 78336-170 | Form: GEL
Manufacturer: Charles and Associates, LLC
Category: otc | Type: HUMAN OTC DRUG LABEL
Date: 20200729

ACTIVE INGREDIENTS: ALCOHOL 71 mL/100 mL
INACTIVE INGREDIENTS: GLYCERIN 0.5 mL/100 mL; CARBOMER 940 8 mL/100 mL; WATER 19.5 mL/100 mL; TROLAMINE 1 mL/100 mL

The hand sanitizer is manufactured using only the following United States Pharmacopoeia (USP) grade ingredients in the preparation of the product (percentage in final product formulation):

1. Alcohol (71%, v/v) in an aqueous solution denatured according to Alcohol and Tobacco Tax and Trade Bureau regulations in 27 CFR part 20.
2. Glycerol (0.5% v/v).
3. Carbomer (8.0% v/v).
4. Trolamine (1.0% v/v).
5. Sterile distilled water or boiled cold water.

Active Ingredient(s)

Ethyl Alcohol 70% v/v. Purpose: Antiseptic

Purpose

Antiseptic

Use

Hand Sanitizer to help reduce bacteria on the skin that potentially can cause sickness, recommended for repeated use.

Warnings

For external use only. Flammable. Keep away from heat and flame.

WHEN USING

Avoid contact with eyes, ears, and mouth. If contact does occur, flush with water.

Stop use and ask a doctor if irritation and redness develop and persists for more than 72 hours.
Keep out of reach of children. If swallowed, get medical help, or contact poison control center right away.

Stop use and ask a doctor if irritation and redness develop and presists for more than 72 hours.

Keep out of reach of children. If swallowed, get medical help, or contact poison control center right away.

Directions

- Apply a small amount to palms, rubbing briskly to cover both hands until dry - repeat as necessary.
- Supervise children under 6 years with the use of this product. Do not use on infants.

Other information

- Store at room temperature
- May discolor certain fabrics
- Harmful to wood finishes and plastics

Inactive ingredients

Deminerialized water, Carbopol 960, Triethanolamine, Glycerin

Package Label - Principal Display Panel

1 gallon / 128 fl oz (3.79 liters) NDC: 78336-070-37

16.9 fl oz (500 ml) NDC: 78336-070-16

8.45 fl oz (250 ml) NDC: 78336-070-08

4.06 fl oz (120 ml) NDC: 78336-070-04

2.03 fl oz (60 ml) NDC: 78336-070-02

1 fl oz (30 ml) NDC: 78336-070-01

1 liter (1000ml) 33.8 fl oz NDC: 78336-070-10